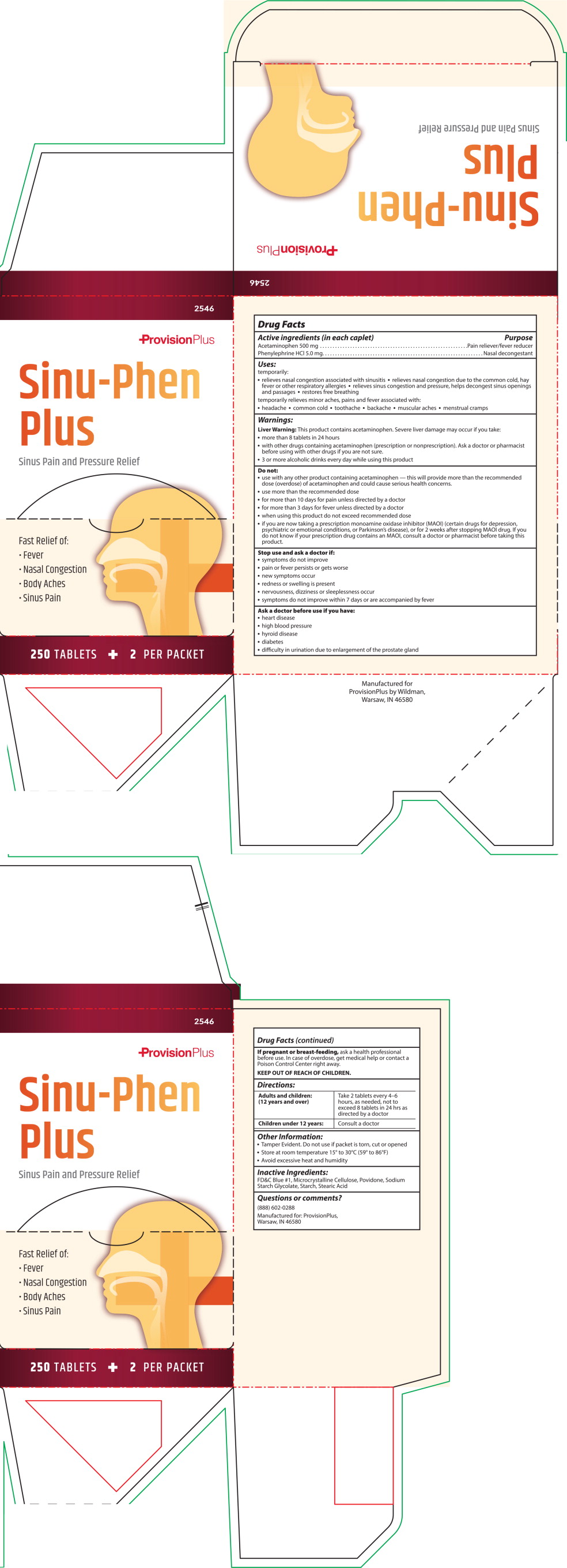 DRUG LABEL: Sinu-Phen Plus 
NDC: 84269-2546 | Form: TABLET
Manufacturer: Wildman Business Group
Category: otc | Type: HUMAN OTC DRUG LABEL
Date: 20260112

ACTIVE INGREDIENTS: ACETAMINOPHEN 500 mg/1 1; PHENYLEPHRINE HYDROCHLORIDE 5 mg/1 1
INACTIVE INGREDIENTS: CROSPOVIDONE (120 .MU.M); POVIDONE; CELLULOSE, MICROCRYSTALLINE; HYPROMELLOSES; POLYETHYLENE GLYCOL, UNSPECIFIED; STARCH, CORN; STEARIC ACID

ACTIVE INGREDIENT

Active ingredients (in each tablet)

Acetaminophen 500mg

Phenylephrine HCl 5mg

PURPOSE

Pain reliever/fever reducer

Nasal decongestant

INDICATIONS & USAGE

Uses

temporarily relieves these common cold/flu symptoms:

nasal congestion

headache

minor aches and pains

stuffy nose

sinus congestion and pressure

temporarily reduces fever

WARNINGS

Liver warning: This product contains acetaminophen. Severe liver damage may occur if you take:

- more than 4,000 mg of acetaminophen in 24 hours
- with other drugs containing acetaminophen
- 3 or more alcoholic drinks every day while using this product

Allergy alert: Acetaminophen may cause severe skin reactions. Symptoms may include:

- skin reddening
- blisters
- rash

If a skin reaction occurs, stop use and seek medical help right away.

DO NOT USE

- with any other drug containing acetaminophen (prescription or nonprescription). If you are not sure whether a drug contains acetaminophen, ask a doctor or pharmacist.
- if you are now taking a prescription monoamine oxidase inhibitor (MAOI) (certain drugs for depression, psychiatric or emotional conditions, or Parkinson's disease), or for 2 weeks after stopping the MAOI drug. If you do not know if your prescription drug contains an MAOI, ask a doctor or pharmacist before taking this product.
- for more than 10 days unless directed by a doctor

ASK DOCTOR

Ask a doctor before use if you have

- liver disease
- thyroid disease
- diabetes
- high blood pressure
- heart disease
- trouble urinating due to an enlarged prostate gland

ASK DOCTOR/PHARMACIST

Ask a doctor or pharmacist before use if you are

- taking the blood thinning drug warfarin

WHEN USING

When using this product do not exceed recommended dosage.

STOP USE

Stop use and ask a doctor if

- you get nervous, dizzy, or sleepless
- pain or nasal congestion gets worse or lasts more than 7 days
- fever gets worse or lasts more than 3 days
- redness or swelling is present
- new symptoms appear

These could be signs of a serious condition.

PREGNANCY OR BREAST FEEDING

If pregnant or breast-feeding, ask a health professional before use.

KEEP OUT OF REACH OF CHILDREN

Overdose warning:

In case of overdose, get medical help or contact a Poison Control Center right away (1-800-222-1222). Quick medical attention is critical for adults as well as for children even if you do not notice any signs or symptoms.

DOSAGE & ADMINISTRATION

Directions

- do not use more than directed

Adults and children: (12 years and over) Take 2 tablets every 6 hours. Do not take more than 8 tablets in 24 hours.

Children under 12 years: Ask a doctor

OTHER SAFETY INFORMATION

Other information

- store at room temperature 59º-86ºF (15º-30ºC)
- tamper evident sealed packets
- do not use any opened or torn packets
- avoid excessive heat and humidity

INACTIVE INGREDIENT

Inactive ingredients

corn starch, crospovidone, hypromelloses, microcrystalline cellulose, polyethylene glycol, povidone, pregelatinized starch, stearic acid.

QUESTIONS

Questions or comments? (888) 602-0288

PRINCIPAL DISPLAY PANEL – 250 Tablet Box Label

ProvisionPlus

Sinu-Phen Plus

Sinus Pain & Pressure Relief

Fast Relief of:

- Fever
- Nasal Congestion
- Body Aches
- Sinus Pain

250 tablets

2 Per Packet